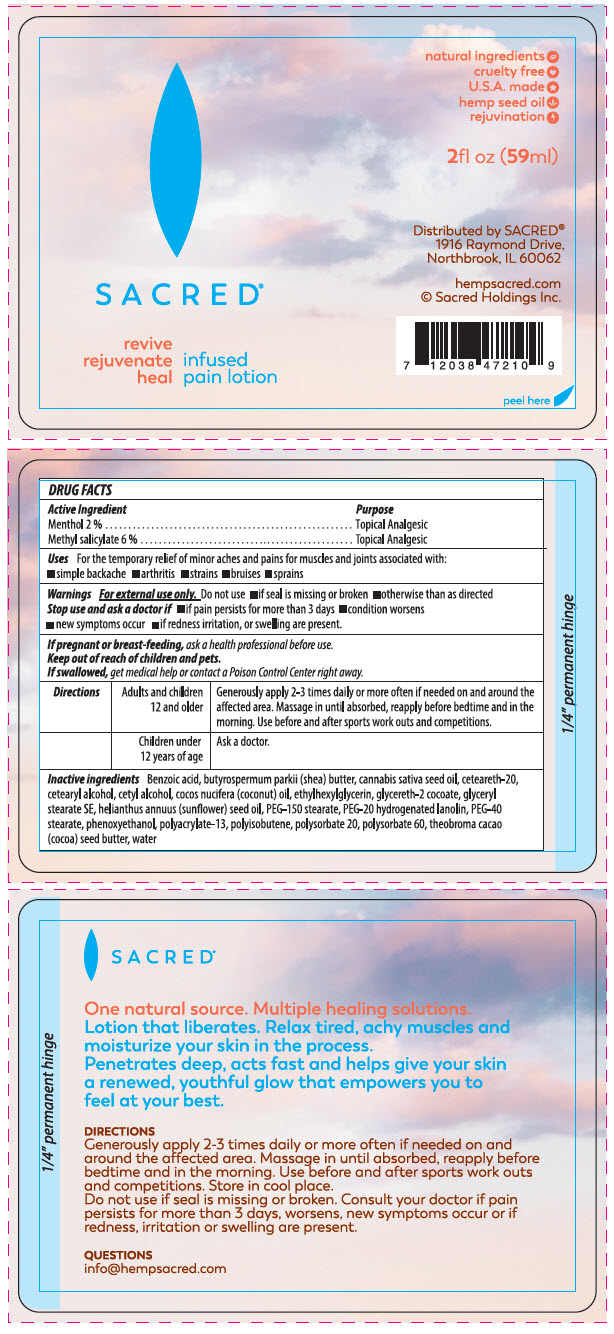 DRUG LABEL: Hemp Pain
NDC: 73616-210 | Form: LOTION
Manufacturer: Sacred Enterprises, LLC
Category: otc | Type: HUMAN OTC DRUG LABEL
Date: 20200324

ACTIVE INGREDIENTS: MENTHOL, UNSPECIFIED FORM 2 mg/100 mL; Methyl Salicylate 6 mg/100 mL
INACTIVE INGREDIENTS: SHEA BUTTER; Benzoic Acid; Cannabis Sativa Seed Oil; POLYOXYL 20 CETOSTEARYL ETHER; Cetyl Alcohol; COCONUT OIL; ETHYLHEXYLGLYCERIN; GLYCERETH-20 COCOATE; Glyceryl Stearate SE; SUNFLOWER OIL; Peg-20 Hydrogenated Lanolin; Peg-40 Stearate; PEG-150 STEARATE; Phenoxyethanol; POLYACRYLAMIDE (1300000 MW); POLYISOBUTYLENE (1000 MW); Polysorbate 20; Polysorbate 60; COCOA BUTTER; CETOSTEARYL ALCOHOL; water

Hemp Pain Lotion

Drug Facts for Sacred Hemp Pain Lotion

ACTIVE INGREDIENT

Active Ingredient | Purpose
Menthol 2% | Topical Analgesic
Methyl Salicylate 6% | Topical Analgesic

Uses

For the temporary relief of minor aches and pains for muscles and joints associated with :

- Simple backache
- arthritis
- strains
- bruises
- sprains

Warnings

For external use only Do not use

- if seal is missing or broken
- otherwise than as directed

Stop use and ask a doctor

- if pain persists for more than 3 days
- condition worsens
- New symptoms occur
- if redness irritation or swelling are present

PREGNANCY OR BREAST FEEDING

If pregnant or breast-feeding, ask a health professional before use

Keep out of reach of children and pets.

If swallowed , get medical help or contact a Poison Control Center right away.

DOSAGE AND ADMINISTRATION

Directions | Adults and children 12 and older | Generously apply 2-3 times daily or more often if needed on and around the affected area. Massage in until absorbed, reapply before bedtime and in the morning. Use before and after sports work outs and competitions.
 | Children under 12 years of age | Ask a doctor.

Inactive ingredients

Benzoic acid, Butyrospermum parkii (shea) butter, Cannabis sativa seed oil, Ceteareth-20,cetearyl alcohol, Cetyl alcohol, Cocos Nucifera (coconut) oil, Ethylhexylglycerin, Glycereth 2 cocoate, Glyceryl stearate SE, Helianthus annuus (sunflower) seed oil , PEG -150 stearate, PEG-20 hydrogenated lanolin, PEG-40 stearate, Phenoxyethanol polyacrulate-13, Polyisobutene, Polysorbate 20, Polysorbate 60, Theobroma cacao (cocoa) seed butter, Water.

QUESTIONS

info@hempsacred.com

Distributed by SACRED®
1916 Raymond Drive,
Northbrook, IL 60062

PRINCIPAL DISPLAY PANEL - 59 ml Bottle Label

SACRED®

revive
rejuvenate
heal

infused
pain lotion